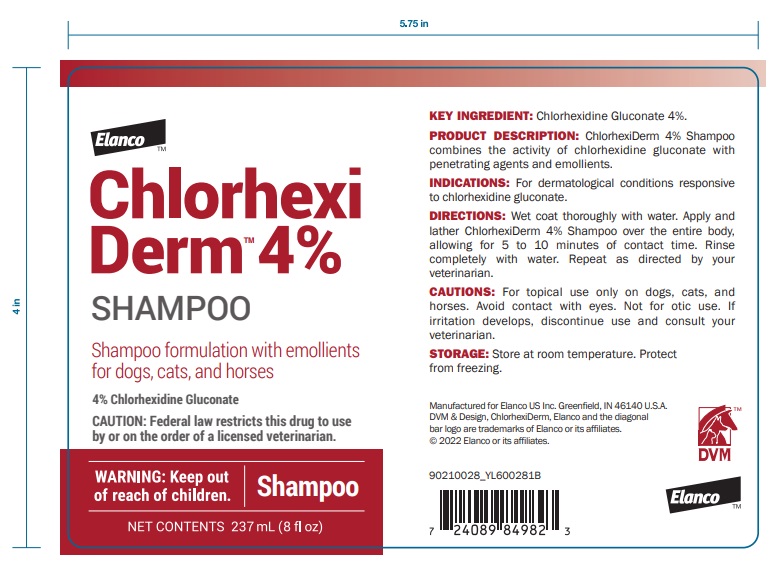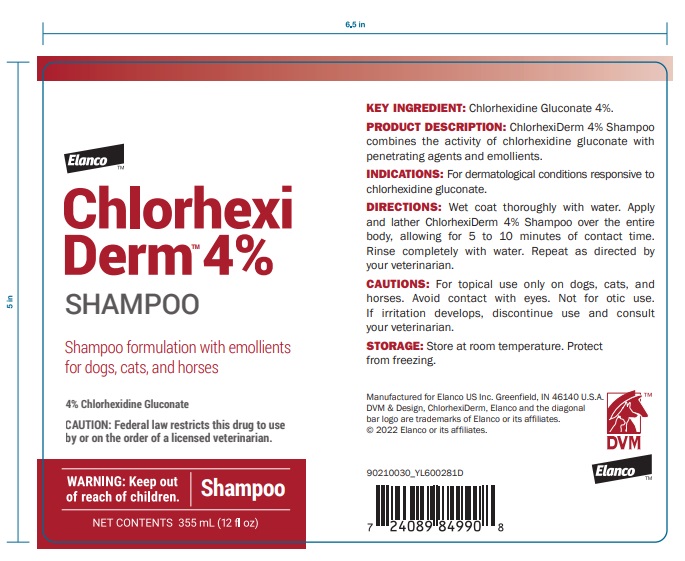 DRUG LABEL: ChlorhexiDerm 4%
NDC: 58198-0016 | Form: SHAMPOO
Manufacturer: Elanco US Inc.
Category: animal | Type: PRESCRIPTION ANIMAL DRUG LABEL
Date: 20230606

ACTIVE INGREDIENTS: CHLORHEXIDINE GLUCONATE 212.0 mg/1 mL

KEY INGREDIENT:

Chlorhexidine Gluconate 4%.

PRODUCT DESCRIPTION:

ChlorhexiDerm 4% Shampoo combines the activity of chlorhexidine gluconate with penetrating agents and emollients.

INDICATIONS:

For dermatological conditions responsive to chlorhexidine gluconate.

DIRECTIONS:

Wet coat thoroughly with water. Apply and lather ChlorhexiDerm 4% Shampoo over the entire body, allowing for 5 to 10 minutes of contact time. Rinse completely with water. Repeat as directed by your veterinarian.

CAUTIONS:

For topical use only on dogs, cats, and horses. Avoid contact with eyes. Not for otic use. If irritation develops, discontinue use and consult your veterinarian.

STORAGE:

Store at room temperature. Protect from freezing.

Manufactured for Elanco US Inc. Greenfield, IN 46140 U.S.A.

DVM & Design, ChlorhexiDerm, Elanco and the diagonal bar logo are trademarks of Elanco or its affiliates.

© 2022 Elanco or its affiliates.

Elanco™

Principal Display Panel - 237 mL Bottle Label

Chlorhexi
Derm™ 4%
SHAMPOO

Shampoo formulation with emollients
for dogs, cats, and horses

4% Chlorhexidine Gluconate

CAUTION: Federal law restricts this drug to use
by or on the order of a licensed veterinarian.

WARNING: Keep out
of reach of children.

Shampoo

NET CONTENTS 237 mL (8 fl oz)

Principal Display Panel - 355 mL Bottle Label

Chlorhexi
Derm™ 4%
SHAMPOO

Shampoo formulation with emollients
for dogs, cats, and horses

4% Chlorhexidine Gluconate

CAUTION: Federal law restricts this drug to use
by or on the order of a licensed veterinarian.

WARNING: Keep out
of reach of children.

Shampoo

NET CONTENTS 355 mL (12 fl oz)